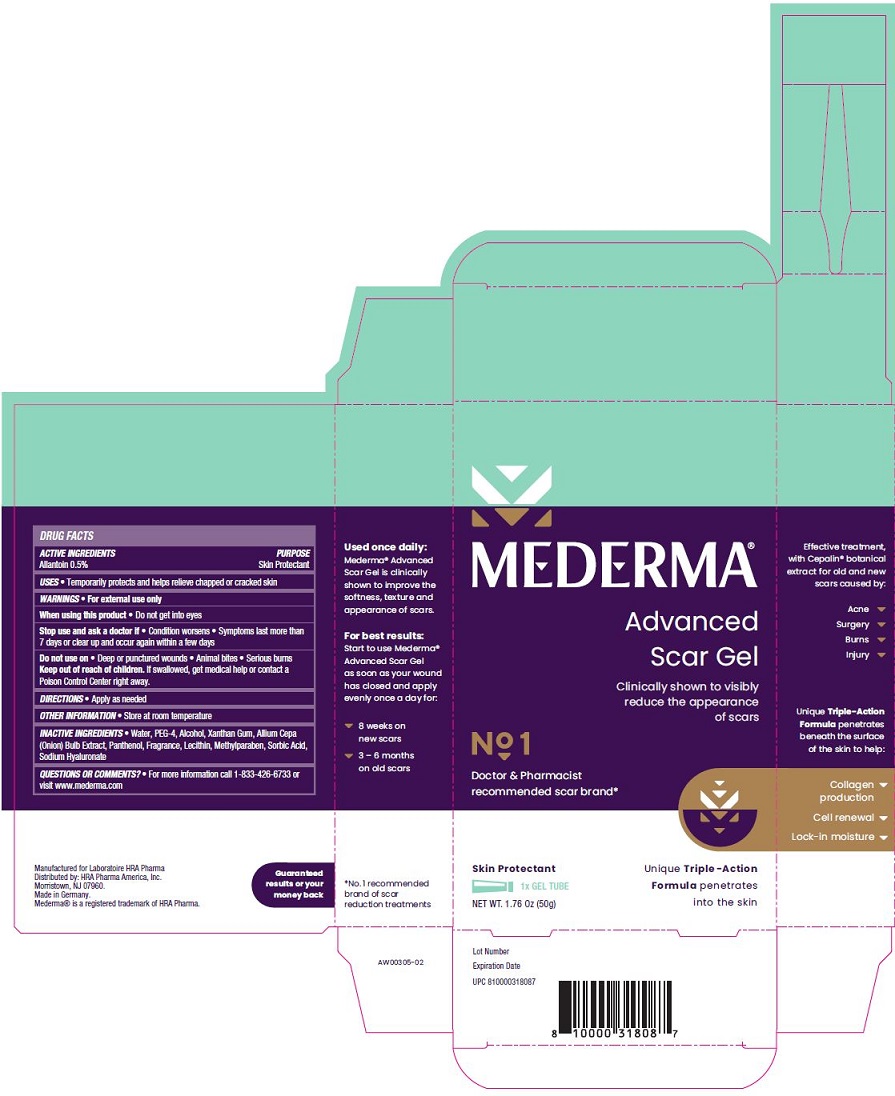 DRUG LABEL: Mederma Advanced Scar
NDC: 73302-201 | Form: GEL
Manufacturer: HRA PHARMA AMERICA, INC.
Category: otc | Type: HUMAN OTC DRUG LABEL
Date: 20250127

ACTIVE INGREDIENTS: Allantoin 5 mg/1 g
INACTIVE INGREDIENTS: Water; Polyethylene Glycol 200; Alcohol; Xanthan Gum; Onion; Sorbic Acid; Panthenol; Egg Phospholipids; Methylparaben; Hyaluronate Sodium

MEDERMA® Advanced Scar Gel DRUG FACTS

Active Ingredients

Allantoin 0.5%

Purpose

Skin Protectant

Uses

- Temporarily protects and helps relieve chapped or cracked skin

Warnings

- For external use only

When using this product

- Do not get into eyes

Stop use and ask a doctor if

- Condition worsens
- Symptoms last more than 7 days or clear up and occur again within a few days

Do not use on

- Deep puncture wounds
- Animal bites
- Serious burns

Keep out of reach of children.

If swallowed, get medical help or contact a Poison Control Center right away.

Directions

- Apply as needed

Other Information

- Store at room temperature

Inactive Ingredients

- Water, PEG-4, Alcohol, Xanthan Gum, Allium Cepa (Onion) Bulb Extract, Panthenol, Fragrance, Lecithin, Methylparaben, Sorbic Acid, Sodium Hyaluronate

Questions or Comments?

- For more information call 1-833-426-6733 or visit www.mederma.com

PRINCIPAL DISPLAY PANEL

MEDERMA® ADVANCED SCAR GEL
Clinically shown to visibly reduce the appearance of scars
No 1 Doctor & Pharmacist recommended scar brand
Skin Protectant

1 x GEL TUBE
NET WT. 1.76 Oz (50g)

Unique Triple-Action Formula penetrates into the skin